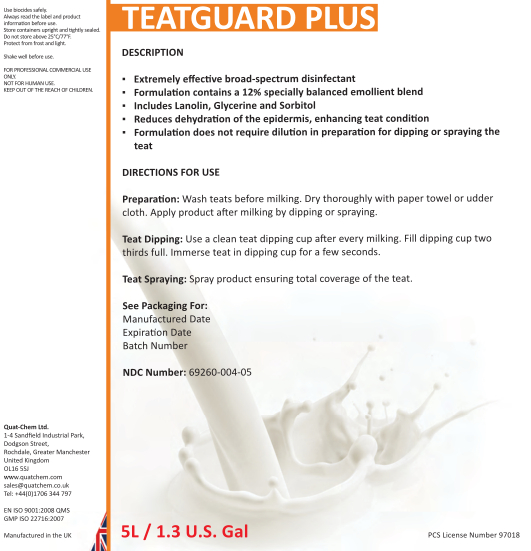 DRUG LABEL: Teatguard Plus
NDC: 69260-008 | Form: LIQUID
Manufacturer: Quat-Chem Ltd.
Category: animal | Type: OTC ANIMAL DRUG LABEL
Date: 20160316

ACTIVE INGREDIENTS: IODINE 5 g/1 L

Teatguard Plus

Teatguard Plus

Use biocides safely.
Always read the label and product information before use.
Store containers upright and tightly sealed.
Do not store above 25°C/77°F.
Protect from frost and light.
Shake well before use.

FOR PROFESSIONAL COMMERCIAL USE
ONLY.
NOT FOR HUMAN USE.
KEEP OUT OF THE REACH OF CHILDREN.

Quat-Chem Ltd.
1-4 Sandfield Industrial Park,
Dodgson Street,
Rochdale, Greater Manchester
United Kingdom
OL16 5SJ
www.quatchem.com
sales@quatchem.co.uk

Tel: +44(0)1706 344 797

EN ISO 9001:2008 QMS
GMP ISO 22716:2007

Manufactured in the UK

DESCRIPTION
▪ Extremely effective broad-spectrum disinfectant
▪ Formulation contains a 12% specially balanced emollient blend
▪ Includes Lanolin, Glycerine and Sorbitol
▪ Reduces dehydration of the epidermis, enhancing teat condition
▪ Formulation does not require dilution in preparation for dipping or spraying the teat

DIRECTIONS FOR USE
Preparation: Wash teats before milking. Dry thoroughly with paper towel or udder cloth. Apply product after milking by dipping or spraying.
Teat Dipping: Use a clean teat dipping cup after every milking. Fill dipping cup two thirds full. Immerse teat in dipping cup for a few seconds.
Teat Spraying: Spray product ensuring total coverage of the teat.

See Packaging For:
Manufactured Date
Expiration Date
Batch Numbe

NDC Number: